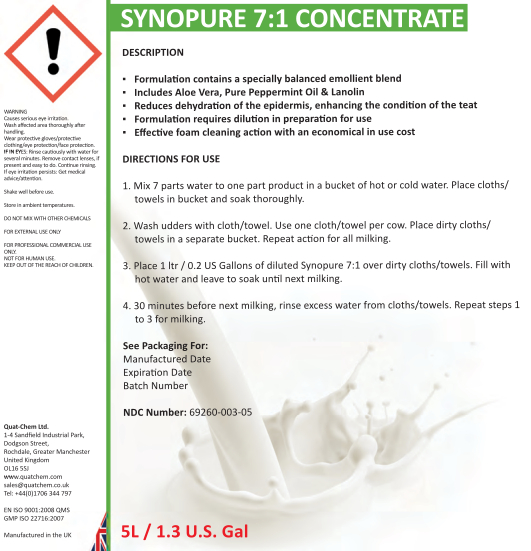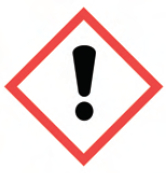 DRUG LABEL: Synopure concentrate
NDC: 69260-003 | Form: LIQUID
Manufacturer: Quat-Chem Ltd.
Category: animal | Type: OTC ANIMAL DRUG LABEL
Date: 20160316

ACTIVE INGREDIENTS: LACTIC ACID 50 g/1 L; BENZALKONIUM CHLORIDE 10.4 1/1 L

Synopure 7:1 concentrate

Synopure 7:1 concentrate

WARNING
Causes serious eye irritation.
Wash affected area thoroughly after handling.
Wear protective gloves/protective clothing/eye protection/face protection.
IF IN EYES: Rinse cautiously with water for several minutes. Remove contact lenses, if present and easy to do. Continue rinsing.
If eye irritation persists: Get medical advice/attention.

Shake well before use.
Store in ambient temperatures.

DO NOT MIX WITH OTHER CHEMICALS
FOR EXTERNAL USE ONLY
FOR PROFESSIONAL COMMERCIAL USE
ONLY.
NOT FOR HUMAN USE.
KEEP OUT OF THE REACH OF CHILDREN.

Quat-Chem Ltd.
1-4 Sandfield Industrial Park,
Dodgson Street,
Rochdale, Greater Manchester
United Kingdom
OL16 5SJ
www.quatchem.com
sales@quatchem.co.uk
Tel: +44(0)1706 344 797
EN ISO 9001:2008 QMS
GMP ISO 22716:2007
Manufactured in the UK

DESCRIPTION
▪ Formulation contains a specially balanced emollient blend
▪ Includes Aloe Vera, Pure Peppermint Oil & Lanolin
▪ Reduces dehydration of the epidermis, enhancing the condition of the teat
▪ Formulation requires dilution in preparation for use
▪ Effective foam cleaning action with an economical in use cost
DIRDIRECTIONS FOR USE
1. Mix 7 parts water to one part product in a bucket of hot or cold water. Place cloths/towels in bucket and soak thoroughly.
2. Wash udders with cloth/towel. Use one cloth/towel per cow. Place dirty cloths/towels in a separate bucket. Repeat action for all milking.
3. Place 1 ltr / 0.2 US Gallons of diluted Synopure 7:1 over dirty cloths/towels. Fill with hot water and leave to soak until next milking.
4. 30 minu minutes before next milking, rinse excess water from cloths/towels. Repeat steps 1 to 3 for milking.

See Packaging For:
Manufactured Date
Expiration Date
Batch Number

NDC Number: